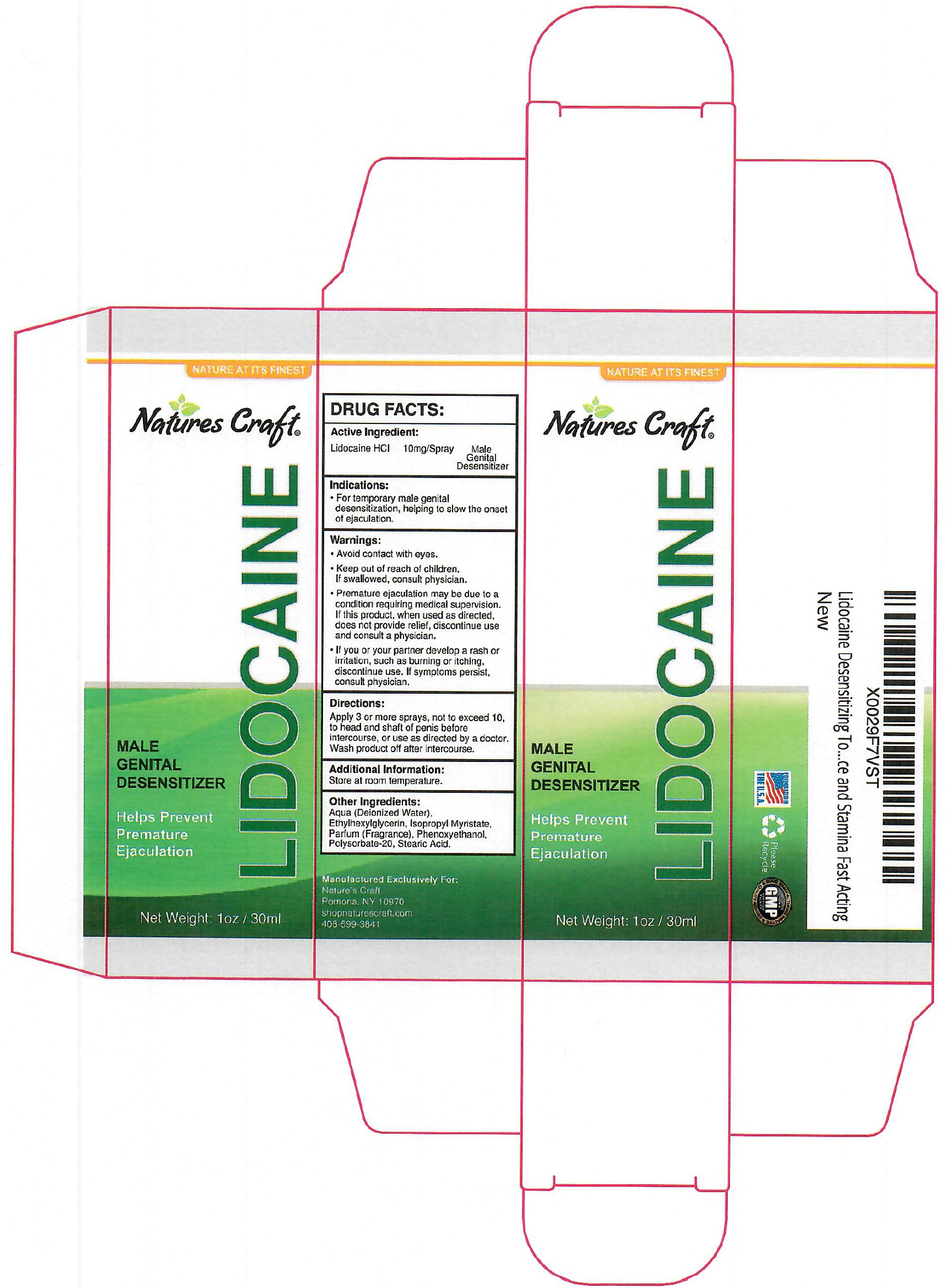 DRUG LABEL: NATURES CRAFT LIDOCAINE Male Genital Desensitizer
NDC: 73382-185 | Form: LIQUID
Manufacturer: Natures Design Products LLC
Category: otc | Type: HUMAN OTC DRUG LABEL
Date: 20231111

ACTIVE INGREDIENTS: LIDOCAINE HYDROCHLORIDE 10 mg/1 mL
INACTIVE INGREDIENTS: WATER; ETHYLHEXYLGLYCERIN; ISOPROPYL MYRISTATE; PHENOXYETHANOL; POLYSORBATE 20; STEARIC ACID

NATURE'S CRAFT LIDOCAINE Male Genital Desensitizer

Active Ingredient:

Lidocaine HCl 10mg/Spray

PURPOSE

Male Genital Desensitizer

Indications:

- For temporary male genital desensitization, helping to slow the onset of ejaculation.

Warnings:

Avoid contact with eyes.

Keep out of reach of children.

- If swallowed, consult physician.
- Premature ejaculation may be due to a condition requiring medical supervision. If this product, when used as directed, does not provide relief, discontinue use and consult a physician.
- If you or your partner develop a rash or irritation, such as burning or itching, discontinue use. If symptoms persist, consult physician.

Directions:

- Apply 3 or more sprays, not to exceed 10, to head and shaft of penis before intercourse, or use as directed by a doctor. Wash product off after intercourse.

Additional Information:

Store at room temperature.

Other Ingredients:

Aqua (Deionized Water), Ethylhexylglycerin, Isopropyl Myristate, Parfum (Fragrance), Phenoxyethanol, Polysorbate-20, Stearic Acid.